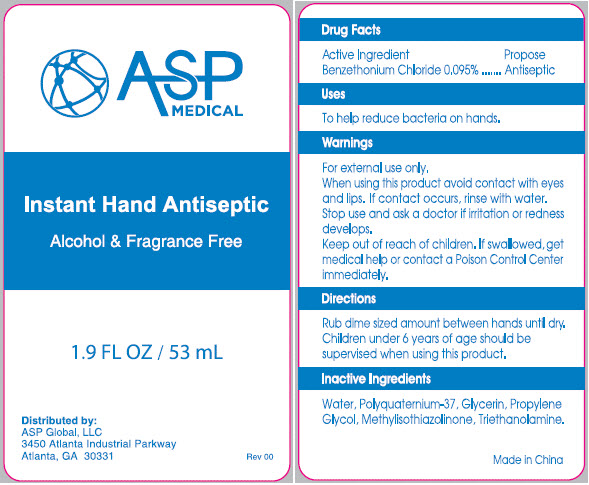 DRUG LABEL: Instant Hand Antiseptic
NDC: 59448-003 | Form: GEL
Manufacturer: ASP Global
Category: otc | Type: HUMAN OTC DRUG LABEL
Date: 20241206

ACTIVE INGREDIENTS: BENZALKONIUM CHLORIDE 0.095 mg/100 mL
INACTIVE INGREDIENTS: WATER; POLYQUATERNIUM-37 (25000 MPA.S); GLYCERIN; PROPYLENE GLYCOL; METHYLISOTHIAZOLINONE; TROLAMINE

Instant Hand Antiseptic

Drug Facts

Active Ingredient

Benzalkonium Chloride 0.095%

Propose

Antiseptic

Uses

To help reduce bacteria on hands.

Warnings

For external use only.

When using this product avoid contact with eyes and lips. If contact occurs, rinse with water.

Stop use and ask a doctor if irritation or redness develops.

Keep out of reach of children. If swallowed, get medical help or contact a Poison Control Center immediately.

Directions

Rub dime sized amount between hands until dry. Children under 6 years of age should be supervised when using this product.

Inactive Ingredients

Water, Polyquatemium-37, Glycerin, Propylene Glycol, Methylisothiazolinone, Trithanolamine.

Distributed by:
ASP Global, LLC
3450 Atlanta Industrial Parkway
Atlanta, GA 30331

PRINCIPAL DISPLAY PANEL - 53 mL Bottle Label

ASP
MEDICAL

Instant Hand Antiseptic

Alcohol & Fragrance Free

1.9 FL OZ / 53 mL

Distributed by:
ASP Global, LLC
3450 Atlanta Industrial Parkway
Atlanta, GA 30331

Rev 00